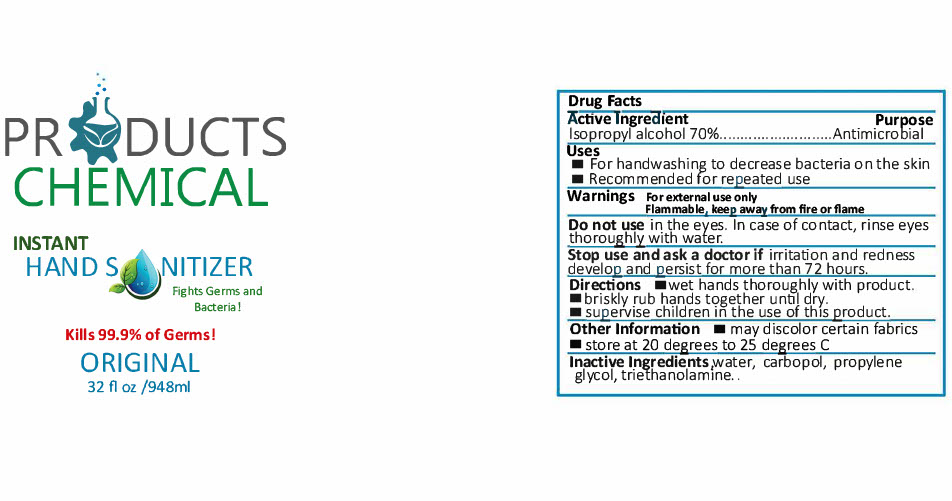 DRUG LABEL: Instant Hand Sanitizer
NDC: 77269-300 | Form: GEL
Manufacturer: Products Chemical Company
Category: otc | Type: HUMAN OTC DRUG LABEL
Date: 20210111

ACTIVE INGREDIENTS: ISOPROPYL ALCOHOL 70 mL/100 mL
INACTIVE INGREDIENTS: TROLAMINE 0.07 mL/100 mL; WATER 31.5 mL/100 mL; PROPYLENE GLYCOL 1 mL/100 mL

This is a hand sanitizer manufactured according to the Temporary Policy for Preparation of Certain Alcohol-Based Hand Sanitizer Products During the Public Health Emergency (CoViD-19); Guidance for Industry.

The hand sanitizer is manufactured using only the following United States Pharmacopoeia (USP) grade ingredients in the preparation of the product (percentage in final product formulation) consistent with World Health Organization (WHO) recommendations:

1. Alcohol (isopropyl) (USP or Food Chemical Codex (FCC) grade) (70%, volume/volume (v/v)) in an aqueous solution denatured according to Alcohol and Tobacco Tax and Trade Bureau regulations in 27 CFR part 20.

Active Ingredient(s)

Alcohol 70% v/v. Purpose: Antiseptic

Purpose

Antiseptic, Hand Sanitizer

Use

Hand Sanitizer to help reduce bacteria that potentially can cause disease. For use when soap and water are not available.

Warnings

For external use only. Flammable. Keep away from heat or flame

Do not use

- in children less than 2 months of age
- on open skin wounds

When using this product keep out of eyes, ears, and mouth. In case of contact with eyes, rinse eyes thoroughly with water.
Stop use and ask a doctor if irritation or rash occurs. These may be signs of a serious condition.
Keep out of reach of children. If swallowed, get medical help or contact a Poison Control Center right away.

Stop use and ask a doctor if irritation or rash occurs. These may be signs of a serious condition.

Keep out of reach of children. If swallowed, get medical help or contact a Poison Control Center right away.

Directions

- Place enough product on hands to cover all surfaces. Rub hands together until dry.
- Supervise children under 6 years of age when using this product to avoid swallowing.

Other information

- Store between 20-25C (68-77F)
- Avoid freezing and excessive heat above 40C (104F)

Inactive ingredients

water, carbopol, propylene glycol, triethanolamine.

Package Label - Prin

948mL NDC: 77269-300-01